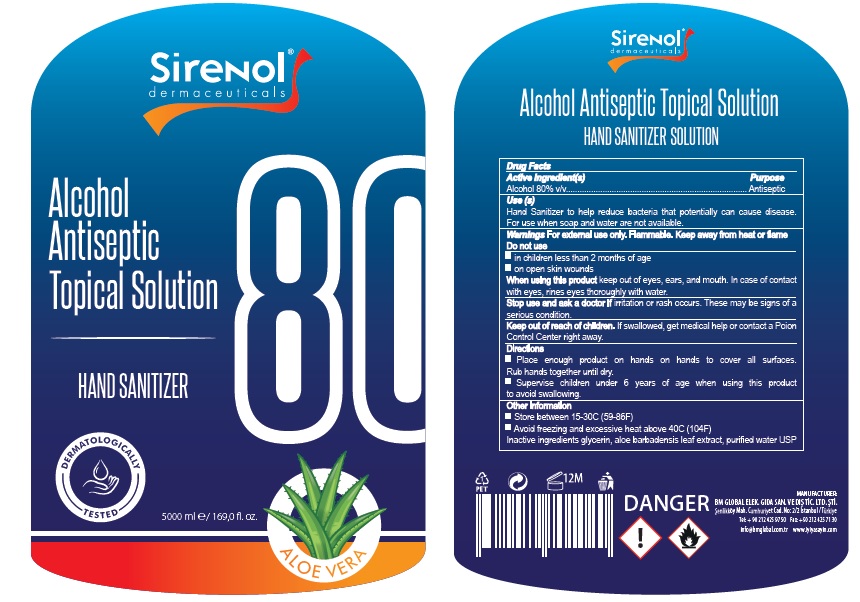 DRUG LABEL: Sirenol Antiseptic Topical
NDC: 80441-001 | Form: SOLUTION
Manufacturer: BM GLOBAL ELEKTRONIK GIDA SANAYI VE DIS TICARET LIMITED SIRKETI
Category: otc | Type: HUMAN OTC DRUG LABEL
Date: 20200902

ACTIVE INGREDIENTS: ALCOHOL 80 mL/100 mL
INACTIVE INGREDIENTS: GLYCERIN; ALOE VERA LEAF; WATER

Sirenol Antiseptic Topical Solution

Active Ingredient

Alcohol 80%v/v

Purpose

Antiseptic

Uses

Hand Sanitizer to help reduce bacteria that potentially can cause disease. For use when soap and water are not available.

Warnings

For external use only. Flammable. Keep away from heat or flame.

Do not use

- in children less than 2 months of age
- on open skin wounds

When using this product keep out of eyes, ears, and mouth. In case of contact with eyes,rines eyes thoroughly with water.

Stop use and ask a doctor if irritation or rash occurs. These may be signs of a serious condition.

Directions

- Place enough product on hands to cover all surfaces. Rub hands together until dry.
- Supervise children under 6 years of age when using this product to avoid swallowing.

Keep out of reach of children

If swallowed, get medical help or contact a Poision Control Center right away.

Other Information (if applicable) :

- Store between 15-30C (59-86F)
- Avoid freezing and excessive heat above 40C^0 (104F^0)

Inactive Ingredient

Glycerin, Aloe Barbadensis Leaf Extract, Purified Water USP.